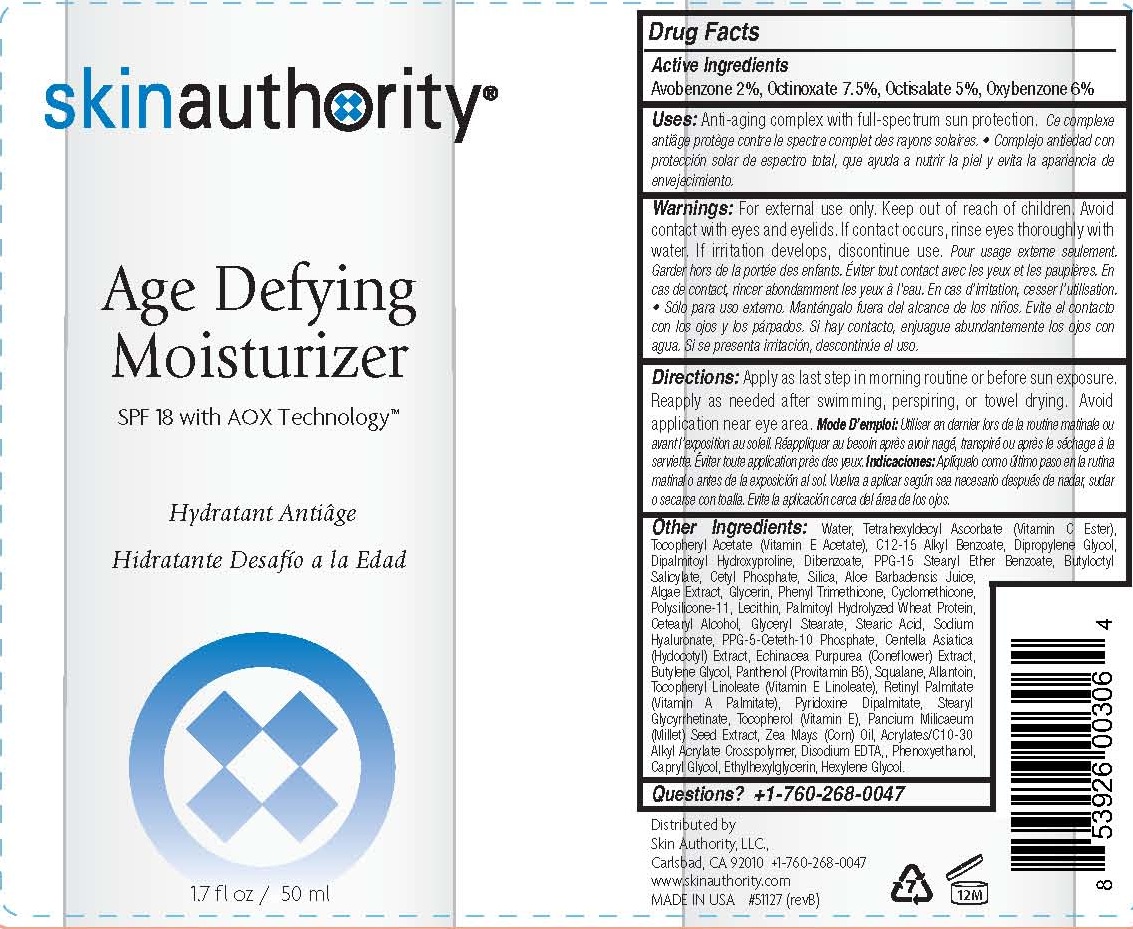 DRUG LABEL: AGE DEFYING MOISTURIZER
NDC: 46007-202 | Form: LOTION
Manufacturer: Skin Authority LLC
Category: otc | Type: HUMAN OTC DRUG LABEL
Date: 20251218

ACTIVE INGREDIENTS: AVOBENZONE 2 g/100 mL; OCTINOXATE 7.5 g/100 mL; OCTISALATE 5 g/100 mL; OXYBENZONE 6 g/100 mL
INACTIVE INGREDIENTS: WATER; TETRAHEXYLDECYL ASCORBATE; ALPHA-TOCOPHEROL ACETATE; ALKYL (C12-15) BENZOATE; DIPROPYLENE GLYCOL DIBENZOATE; PPG-15 STEARYL ETHER BENZOATE; BUTYLOCTYL SALICYLATE; CYCLOMETHICONE; EDETATE DISODIUM; SILICON DIOXIDE; CORN OIL; ALOE VERA LEAF; FUCUS VESICULOSUS; PANTHENOL; DIPALMITOYL HYDROXYPROLINE; TOCOPHEROL; GLYCERIN; CETYL PHOSPHATE; PHENYL TRIMETHICONE; POLYSILICONE-15; LECITHIN, SOYBEAN; CARBOMER INTERPOLYMER TYPE A (ALLYL SUCROSE CROSSLINKED); PHENOXYETHANOL; CAPRYLYL GLYCOL; ETHYLHEXYLGLYCERIN; HEXYLENE GLYCOL; HYDROLYZED WHEAT PROTEIN (ENZYMATIC, 3000 MW); CETOSTEARYL ALCOHOL; GLYCERYL MONOSTEARATE; STEARIC ACID; HYALURONATE SODIUM; PPG-5-CETETH-20; CENTELLA ASIATICA; ECHINACEA PURPUREA; BUTYLENE GLYCOL; SQUALANE; ALLANTOIN; .ALPHA.-TOCOPHEROL LINOLEATE, D-; VITAMIN A PALMITATE; PYRIDOXINE DIPALMITATE; STEARYL GLYCYRRHETINATE; MILLET

Skin Authority - AGE DEFYING MOISTURIZER (46007-202)- delist

ACTIVE INGREDIENTS:

AVOBENZONE 2%, OCTINOXATE 7.5%, OCTISALATE 5%, OXYBENZONE 6%

PURPOSE:

SUNSCREEN

INDICATIONS AND USAGE

USES: ANTI-AGING COMPLEX WITH FULL-SPECTRUM SUN PROTECTION.

WARNINGS:

FOR EXTERNAL USE ONLY.

KEEP OUT OF REACH OF CHILDREN.

OTHER SAFETY INFORMATION

AVOID CONTACT WITH EYES AND EYELIDS. IF CONTACT OCCURS, RINSE EYES THOROUGHLY WITH WATER.

IF IRRITATION DEVELOPS, DISCONTINUE USE.

DIRECTIONS:

APPLY AS LAST STEP IN MORNING ROUTINE OR BEFORE SUN EXPOSURE. REAPPLY AS NEEDED AFTER SWIMMING, PERSPIRING, OR TOWEL DRYING. AVOID APPLICATION NEAR EYE AREA.

OTHER INGREDIENTS:

WATER, TETRAHEXYLDECYL ASCORBATE (VITAMIN C ESTER), TOCOPHERYL ACETATE (VITAMIN E ACETATE), C12-15 ALKYL BENZOATE, DIPROPYLENE GLYCOL DIBENZOATE, DIPALMITOYL HYDROXYPROLINE, PPG-15 STEARYL ETHER BENZOATE, BUTYLOCTYL SALICYLATE, CETYL PHOSPHATE, SILICA, ALOE BARBADENSIS JUICE, ALGAE EXTRACT, GLYCERIN, PHENYL TRIMETHICONE, CYCLOMETHICONE, POLYSILICONE-11, LECITHIN, PALMITOYL HYDROLYZED WHEAT PROTEIN, CETEARYL ALCOHOL, GLYCERYL STEARATE, STEARIC ACID, SODIUM HYALURONATE, PPG-5-CETETH-10 PHOSPHATE, CENTELLA ASIATICA (HYDOCOTYL) EXTRACT, ECHINACEA PURPUREA (CONEFLOWER) EXTRACT, BUTYLENE GLYCOL, PANTHENOL (PROVITAMIN B5), SQUALANE, ALLANTOIN, TOCOPHERYL LINOLEATE (VITAMIN E LINOLEATE), RETINYL PALMITATE (VITAMIN A PALMITATE), PANCIUM MILICAEUM (MILLET) SEED EXTRACT, ZEA MAYS (CORN) OIL, ACRYLATES/C10-30 ALKYL ACRYLATE CROSSPOLYMER, DISODIUM EDTA, PHENOXYETHANOL, CAPRYL GLYCOL, ETHYLHEXYLGLYCERIN, HEXYLENE GLYCOL.

QUESTIONS? +1-760-268-0047